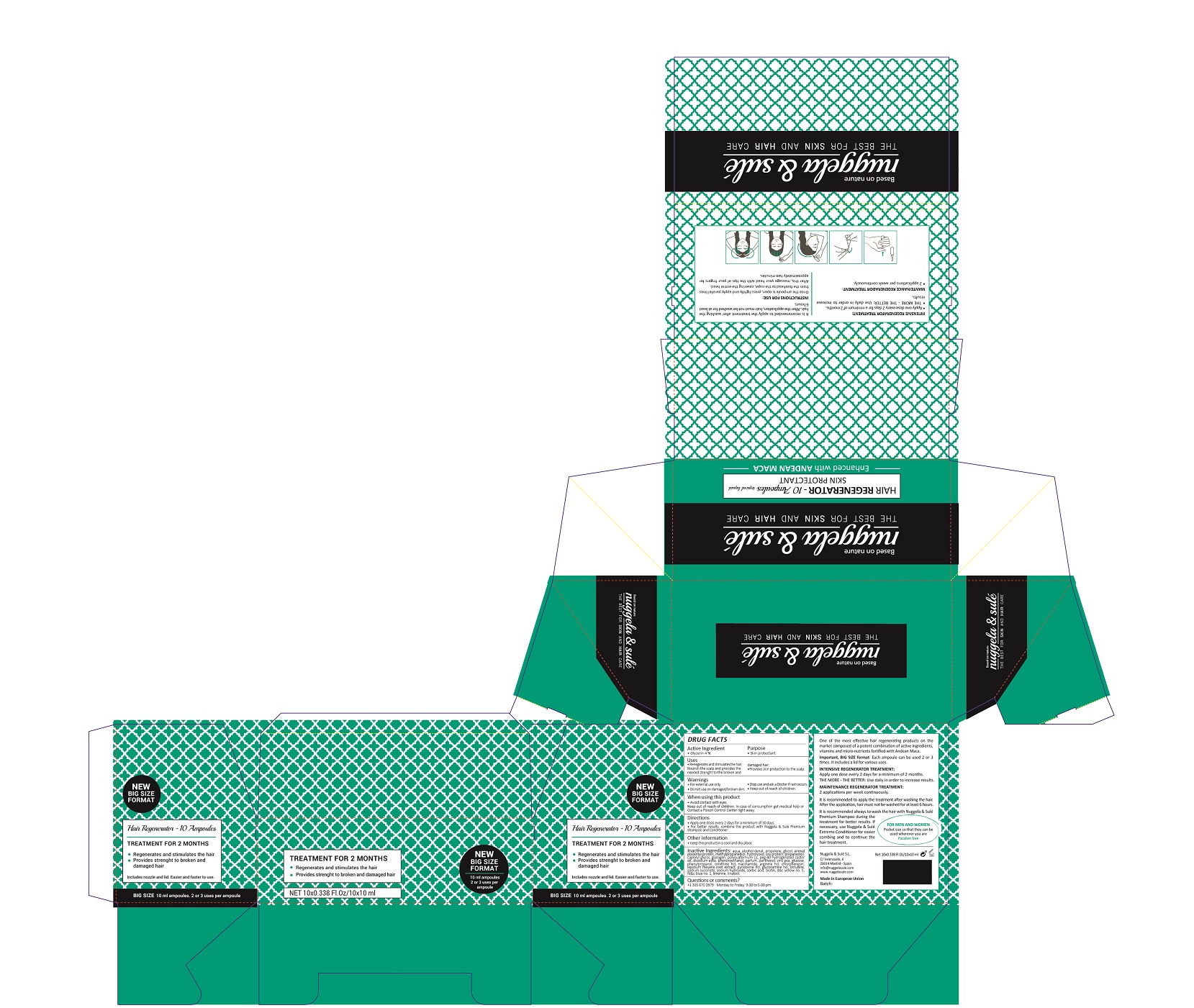 DRUG LABEL: HAIR REGENERATOR
NDC: 71578-001 | Form: SOLUTION
Manufacturer: NUGGELA & SULE SL
Category: otc | Type: HUMAN OTC DRUG LABEL
Date: 20200528

ACTIVE INGREDIENTS: GLYCERIN 4 mg/1 mL
INACTIVE INGREDIENTS: FD&C YELLOW NO. 5 0.0001 mg/1 mL; FD&C BLUE NO. 1 0.0001 mg/1 mL; BIOTIN 0.002 mg/1 mL; LINALOOL, (-)- 0.0001 mg/1 mL; WATER 64.33 mg/1 mL; DIPROPYLENE GLYCOL 6.82 mg/1 mL; PHENOXYETHANOL 0.17 mg/1 mL; HYDROLYZED PLACENTAL PROTEIN (BOVINE) 6.53 mg/1 mL; METHYLPROPANEDIOL 2.4 mg/1 mL; SOY PROTEIN 1.97 mg/1 mL; PROPANEDIOL 0.98 mg/1 mL; LIMONENE, (+)- 0.01 mg/1 mL; CAPRYLYL GLYCOL 0.52 mg/1 mL; GLYCOGEN 0.5 mg/1 mL; POLYQUATERNIUM-11 (1000000 MW) 0.4 mg/1 mL; PEG-40 CASTOR OIL 0.25 mg/1 mL; EDETATE DISODIUM 0.2 mg/1 mL; ZINC PIDOLATE 0.1 mg/1 mL; DEXTROSE 0.1 mg/1 mL; PHENYLPROPANOL 0.07 mg/1 mL; ORNITHINE HYDROCHLORIDE 0.07 mg/1 mL; NIACINAMIDE 0.07 mg/1 mL; ARGININE HYDROCHLORIDE 0.07 mg/1 mL; CHLORPHENESIN 0.03 mg/1 mL; PANTHENOL 0.106 mg/1 mL; LEPIDIUM MEYENII ROOT 0.03 mg/1 mL; PYRIDOXINE HYDROCHLORIDE 0.02 mg/1 mL; GLUCOSAMINE HYDROCHLORIDE 0.02 mg/1 mL; CITRULLINE 0.02 mg/1 mL; SODIUM SUCCINATE HEXAHYDRATE 0.01 mg/1 mL; SODIUM HYDROXIDE 0.0044 mg/1 mL; SORBIC ACID 0.002 mg/1 mL; ALCOHOL 10 mg/1 mL

Hair Regenerator topical solution

ACTIVE INGREDIENTS PURPOSE

Glycerin 4%.................... Skin Protectant

Warnings

For external use only.

Do not use on damaged or broken skin.

Stop use and ask a doctor if rash occurs.

Keep out of reach of children.

Whhen using this product do not get into eyes.

Children under 6 months: as a doctor.

WARNINGS

Stop use and ask a doctor if rash occurs

Children under 6 months: ask a doctor

Warnings

Keep out of reach of children

Questions or comments?

+ 305 670 0979 M-F 9:00 am to 5:00 pm

Other Information

. keep the product in a cool and dry place

Directions

- apply one dose every 2 days for a minimun of 30 days
- for better results, combine this product with Nuggela & Sule Premium shampoo and Conditioner

DOSAGE AND ADMINISTRATION

- apply one dose every 2 days for a minimun of 30 days
- for better results, combine this product with Nuggela & Sule Premium shampoo and Conditioner

Uses

- regenerates and stimulates the hair
- nourish the scalp and provides the needed strenght to the broken and damaged hair
- provides skin protection to the scalp

Inactive Ingredients

AQUA, ALCOHOL DENAT, PROPYLENE GLYCOL, PLACENTAL PROTEIN, METHYLPROPANEDIOL, HYDROLYZED SOY PROTEIN, PROPANEDIOL, CAPRYLYL GLYCOL, GLYCOGEN, POLYQUATERNIUM-11, PEG-40 HYDROGENATED CASTOR OIL

DISODIUM EDTA, PHENOXYETHANOL, PARFUM, PANTHENOL, ZINC PCA, GLUCOSE, PHENYLPROPANOL, ORNITHINE HCL, NIACINAMIDE, ARGININE HCL, CHLORPHENESIN, LEPIDIUM MEYENII ROOT EXTRACT, PYRIDOXINE HCL, GLUCOSAMINE HCL, CITRULLINE, SODIUM SUCCINATE, SODIUM HYDROXIDE,SORBIC ACID, BIOTIN, D&C Yellow No. 5, FD&C Blue No.1, LIMONENE, LINALOOL

Uses

- regenerates and stimulates the hair
- nourish the scalp and provides the needed strenght to the broken and damaged hair
- provides skin protection to the scalp